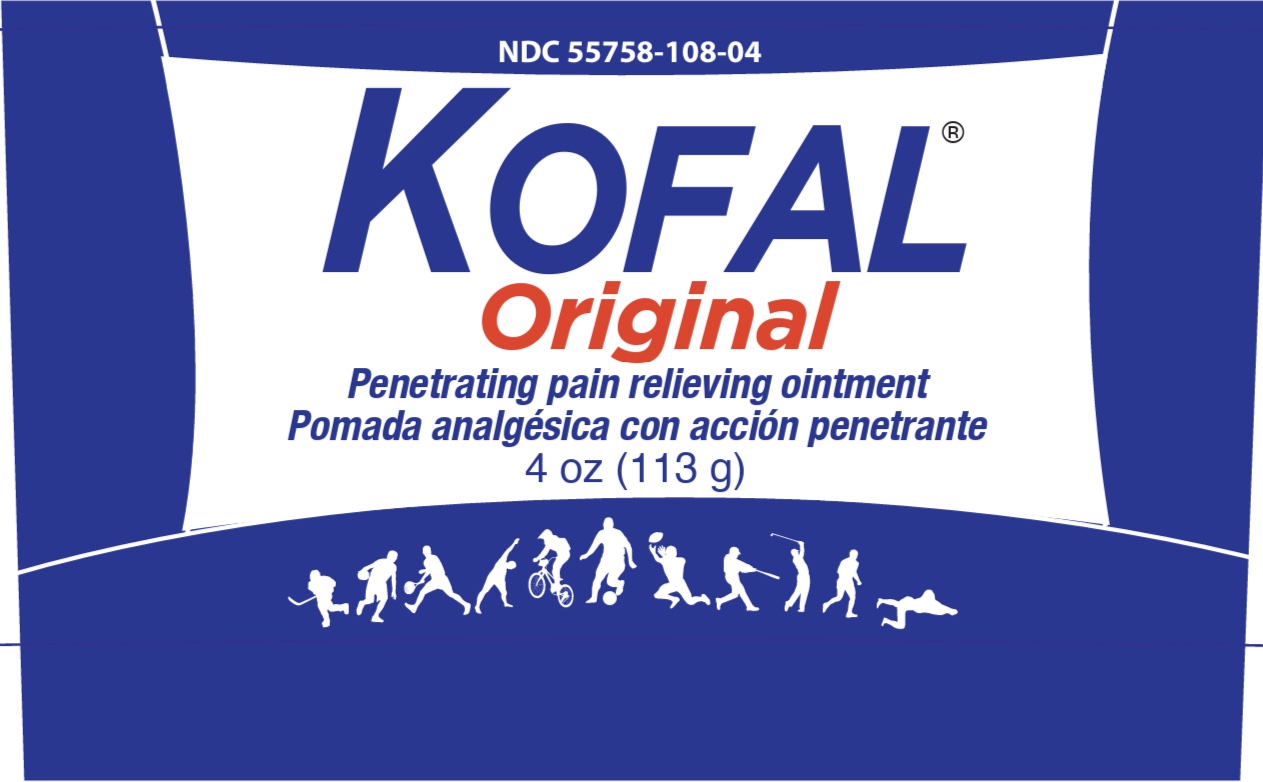 DRUG LABEL: Kofal Original
NDC: 55758-108 | Form: OINTMENT
Manufacturer: Pharmadel LLC
Category: otc | Type: HUMAN OTC DRUG LABEL
Date: 20251204

ACTIVE INGREDIENTS: METHYL SALICYLATE 12 g/100 g
INACTIVE INGREDIENTS: POLYSORBATE 20; GLYCERYL MONOSTEARATE; PROPYLPARABEN; WATER; TROLAMINE; METHYLPARABEN; PARAFFIN; EUCALYPTUS OIL; MENTHOL, UNSPECIFIED FORM; STEARIC ACID; CAMPHOR, (-)-; CETOSTEARYL ALCOHOL

Kofal Original Blue 4 Oz (WP)(DA)

Active ingredient and Purpose

Active ingredient Purpose

Methyl salicylate 12%...........................External analgesic

Uses

For the temporary relief of minor aches and pains of muscles and joints associated with

- simple backache
- arthritis
- strains
- bruises
- sprains

Warnings

For external use only. Avoid contact with the eyes

Do not use

- on wounds or damaged skin

When using this product

- do not bandage tightly

Stop use and ask a doctor if

- condition worsens
- symptoms persist for more than 7 days or clear up and occurs again within a few days

If pregnant or breast feeding,

ask a health professional before use.

If pregnant or breast feeding,

ask a health professional before use.

Keep out of reach of children.

If swallowed, get medical help, or contact a Poison Control Center immediately.

Directions

- adults and children 12 years of age and older: apply to affected area not more than 3 to 4 times daily
- children under 12 years of age: do not use, consult a doctor

Other information

- store between 59-86°F (15-30°C)
- do not use if seal over cap is broken, torn, or missing

Inactive ingredients

camphor, cetostearyl alcohol, eucalyptus oil, glyceryl monostearate, menthol, methylparaben, paraffin, polysorbate 20, propylparaben, stearic acid, trolamine, water